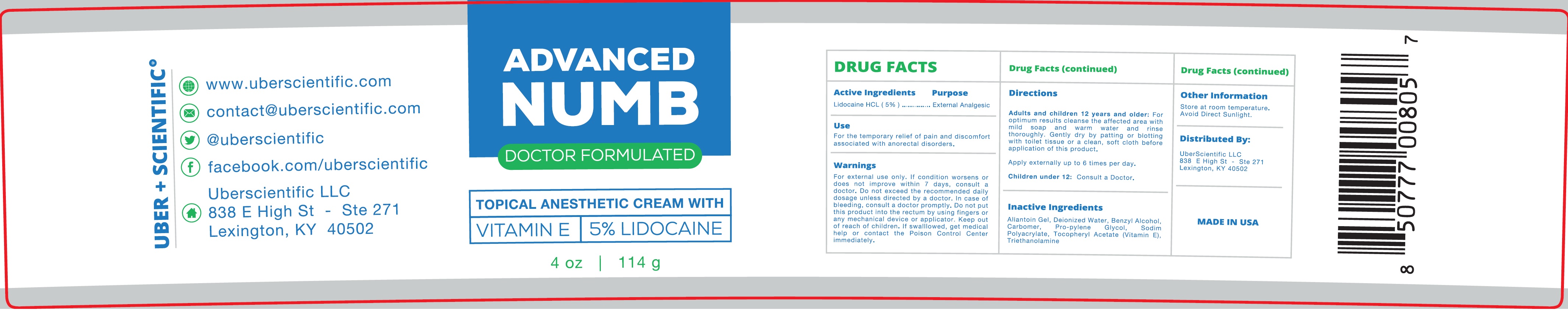 DRUG LABEL: ADVANCED NUMB Topical Anesthetic
NDC: 71131-052 | Form: CREAM
Manufacturer: Uber Scientific, LLC
Category: otc | Type: HUMAN OTC DRUG LABEL
Date: 20231013

ACTIVE INGREDIENTS: LIDOCAINE HYDROCHLORIDE 50 mg/1 g
INACTIVE INGREDIENTS: WATER; BENZYL ALCOHOL; CARBOXYPOLYMETHYLENE; PROPYLENE GLYCOL; .ALPHA.-TOCOPHEROL; TROLAMINE

ADVANCED NUMB Topical Anesthetic

Active Ingredients

Lidocaine HCL (5%)

Purpose

External Analgesic

Use

For the temporary relief of pain and discomfort associated with anorectal disorders.

Warnings

For external use only. If condition worsens or does not improve within 7 days, consult a doctor.

Do not

exceed the recommended daily dosage unless directed by a doctor. In case of bleeding, Consult a doctor promptly. Do not put this product into the rectum by using fingers or any mechanical device or applicator.

Keep out of reach of children.

If swallowed, get medical help or contact the Poison Control Center immediately.

Directions

Adults and children 12 years and older: For optimum results cleanse the affected area with mild soap and warm water and rinse thoroughly. Gently dry by patting or blotting with toilet tissue or a clean, soft cloth before application of this product.

Apply externally up to 6 times per day.

Children under 12: Consult a Doctor.

Inactive ingredients

Allantoin Gel, Deionized Water, Benzyl Alcohol, Carbomer, Pro-pylene GLycol, Sodim Polyacrylate, Tocopheryl Acetate (Vitamin E), Triethanolamine

Other Information

Store at room temperature. Avoid Direct sunlight.